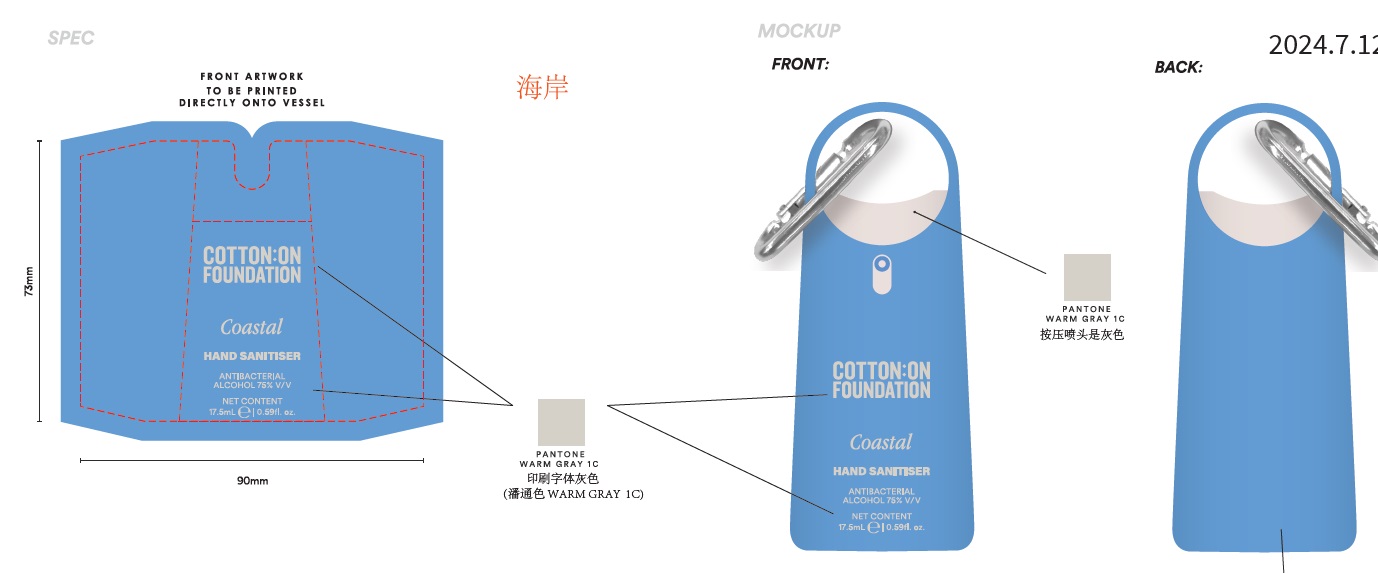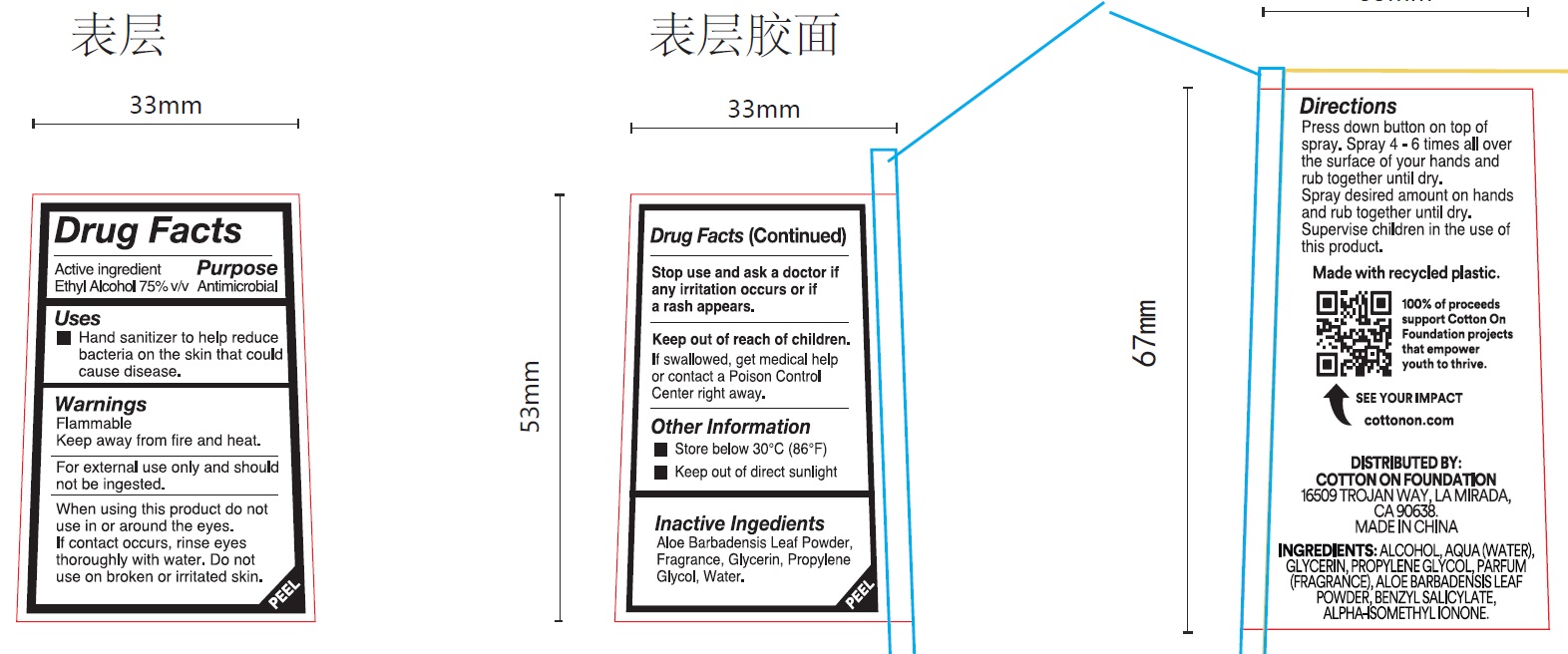 DRUG LABEL: COTTON ON FOUNDATION Coastal Hand Sanitizer
NDC: 43473-052 | Form: SPRAY
Manufacturer: Nantong Health & Beyond Hygienic Products Inc.
Category: otc | Type: HUMAN OTC DRUG LABEL
Date: 20240904

ACTIVE INGREDIENTS: ALCOHOL 75 mL/100 mL
INACTIVE INGREDIENTS: WATER; GLYCERIN; PROPYLENE GLYCOL; ALOE VERA LEAF

43473-052 COTTON ON FOUNDATION Coastal Hand Sanitizer

Active ingredient

Ethyl Alcohol, 75% v/v

Purpose Antimicrobial

Uses

- Hand sanitizer to help reduce baterial on the skin that could cause diseases.

Warnings

For external use only and should not be ingested.

Flammable, keep away from fire and heat

When using this product, do not use in or around the eyes. If contact occurs, rinse eyes thoroughly with water. Do not use on broken or irritated skin.

Stop use and ask a doctor if any irritation occurs or if a rash appears.

Keep out of reach of children. If swallowed, get medical help or contact a Poison Control Center right away.

Directions

Press down button on top of spray. Spray 4-6 times all over the surface of your hands and rub together until dry.
Spray desired amount on hands and rub together until dry.
Supervise children in the use of this product

Other information

Store below 30C (86F)

Keep out of direct sunlight

Inactive ingredients

Aloe Barbadensis Leaf Powder, Fragrance(Parfum), Glycerin, Propylene Glycol, Water